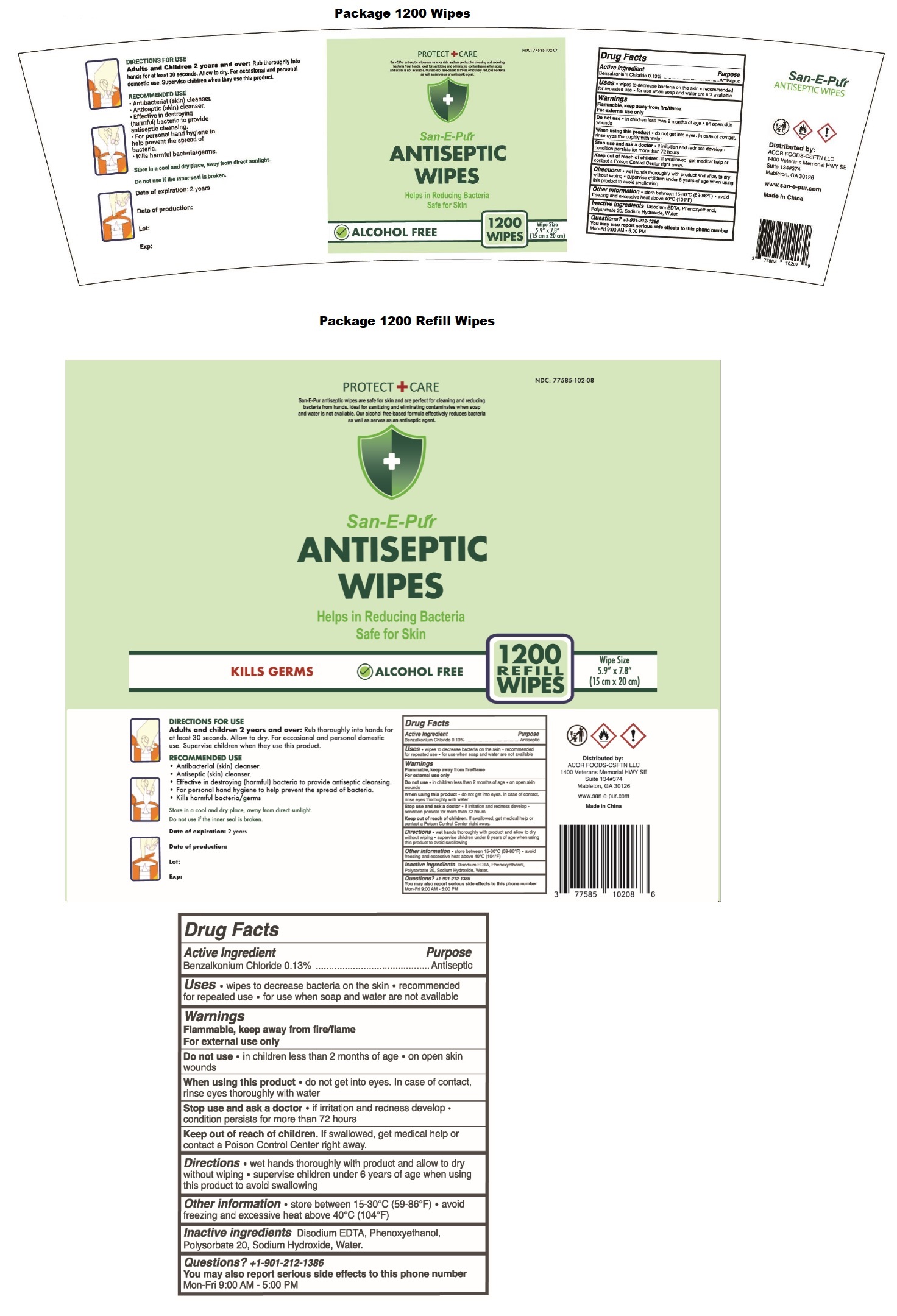 DRUG LABEL: San-E-Pur ANTISEPTIC WIPES
NDC: 77585-102 | Form: CLOTH
Manufacturer: Acor Foods-csftn Llc
Category: otc | Type: HUMAN OTC DRUG LABEL
Date: 20201016

ACTIVE INGREDIENTS: BENZALKONIUM CHLORIDE 0.13 g/100 g
INACTIVE INGREDIENTS: EDETATE DISODIUM ANHYDROUS; PHENOXYETHANOL; POLYSORBATE 20; SODIUM HYDROXIDE; WATER

San-E-Pur ANTISEPTIC WIPES

Active Ingredient

Benzalkonium Chloride 0.13%

Purpose

Antiseptic

INDICATIONS AND USAGE

Uses • wipes to decrease bacteria on the skin • recommended for repeated use • for use when soap and water are not available

Warnings

Flammable, keep away from fire/flame
For external use only

Do not use • in children less than 2 months of age • on open skin wounds

When using this product • do not get into eyes. In case of contact, rinse eyes thoroughly with water

Stop use and ask a doctor • if irritation and redness develop • condition persists for more than 72 hours

Keep out of reach of children. If swallowed, get medical help or contact a Poison Control Center right away.

DOSAGE AND ADMINISTRATION

Directions • wet hands thoroughly with product and allow to dry without wiping • supervise children under 6 years of age when using this product to avoid swallowing

Other information • store between 15-30°C (59-86°F) • avoid freezing and excessive heat above 40°C (104°F)

INACTIVE INGREDIENT

Inactive ingredients Disodium EDTA, Phenoxyethanol, Polysorbate 20, Sodium Hydroxide, Water

Questions?

+1-901-212-1386

You may also report serious side effects to this phone number.
Mon-Fri 9:00 AM - 5:00 PM

PROTECT CARE

San-E-Pur antiseptic wipes are safe for skin and are perfect for cleaning and reducing bacteria from hands.
Ideal for sanitizing and eliminating contaminates when soap and water is not available. Our alcohol free-based
formula effectively reduces bacteria as well as serves as an antiseptic agent

Helps In Reducing Bacteria Safe for Skin

KILLS GERMS

ALCOHOL FREE

Wipe Size

(5.9" x 7.8")
(15 cm x 20 cm)

DIRECTIONS FOR USE

Adults and children 2 years and over: Rub thoroughly into hands for at least 30 seconds. Allow to dry. For occasional and personal domestic use. Supervise children when they use this product.

RECOMMENDED USE

- Antibacterial (skin) cleanser.
- Antiseptic (skin) cleanser.
- Effective in destroying (harmful) bacteria to provide antiseptic cleansing.
- For personal hand hygiene to help prevent the spread of bacteria.
- Kills harmful bacteria/germs.

Store in a cool and dry place, away from direct sunlight.

Do not use if the inner seal is broken.

Distributed by:
ACOR FOODS-CSFTN LLC
1400 Veterans Memorial HWY SE
Suite 134#374
Mableton, GA 30126

www.san-e-pur.com

made in China